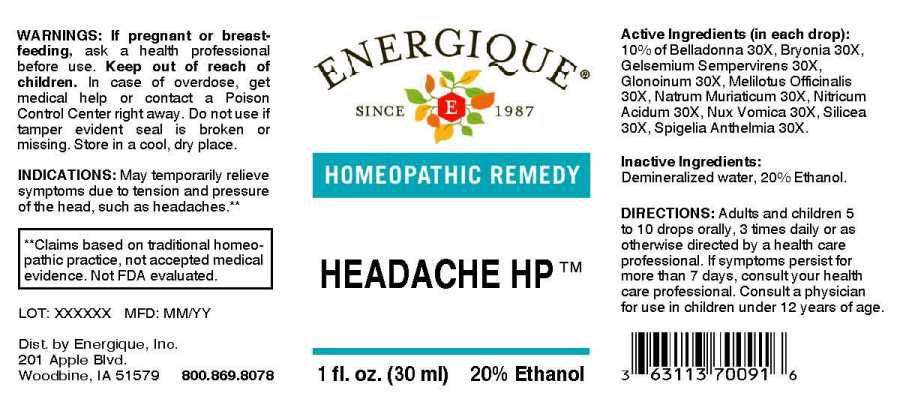 DRUG LABEL: Headache
NDC: 44911-0071 | Form: LIQUID
Manufacturer: Energique, Inc.
Category: homeopathic | Type: HUMAN OTC DRUG LABEL
Date: 20240326

ACTIVE INGREDIENTS: ATROPA BELLADONNA WHOLE 30 [hp_X]/1 mL; BRYONIA ALBA ROOT 30 [hp_X]/1 mL; GELSEMIUM SEMPERVIRENS ROOT 30 [hp_X]/1 mL; NITROGLYCERIN 30 [hp_X]/1 mL; MELILOTUS OFFICINALIS TOP 30 [hp_X]/1 mL; SODIUM CHLORIDE 30 [hp_X]/1 mL; NITRIC ACID 30 [hp_X]/1 mL; STRYCHNOS NUX-VOMICA SEED 30 [hp_X]/1 mL; SILICON DIOXIDE 30 [hp_X]/1 mL; SPIGELIA ANTHELMIA WHOLE 30 [hp_X]/1 mL
INACTIVE INGREDIENTS: WATER; ALCOHOL

DRUG FACTS:

ACTIVE INGREDIENTS

(in each drop):10% of Belladonna 30X, Bryonia 30X, Gelsemium Sempervirens 30X, Glonoinum 30X, Melilotus Officinalis 30X, Natrum Muriaticum 30X, Nitricum Acidum 30X, Nux Vomica 30X, Silicea 30X, Spigelia Anthelmia 30X.

INDICATIONS

May temporary relieve symptoms due to tension and pressure of the head, such as headache.**

**Claims based on traditional homeopathic practice, not accepted medical evidence. Not FDA evaluated.

WARNINGS

If pregnant or breast-feeding, ask a health professional before use.

Keep out of reach of children. In case of overdose, get medical help or contact a Poison Control Center right away.

Do not use if tamper evident seal is broken or missing. Store in a cool, dry place.

KEEP OUT OF REACH OF CHILDREN

In case of overdose, get medical help or contact a Poison Control Center right away.

DIRECTIONS

Adults and children 5 to 10 drops orally, 3 times daily or as otherwise directed by a health care professional. If symptoms persist for more than 7 days, consult your health care professional. Consult a physician for use in children under 12 years of age.

INDICATIONS AND USAGE

May temporary relieve symptoms due to tension and pressure of the head, such as headache.**

**Claims based on traditional homeopathic practice, not accepted medical evidence. Not FDA evaluated.

INACTIVE INGREDIENTS

Demineralized water, 20% Ethanol.

QUESTIONS

Dist. by Energique, Inc.

201 Apple Blvd

Woodbine, IA 51579

800-869-8078

PACKAGE LABEL

ENERGIQUE

since 1987

HOMEOPATHIC REMEDY

HEADACHE HP

1 fl. oz. (30 ml)